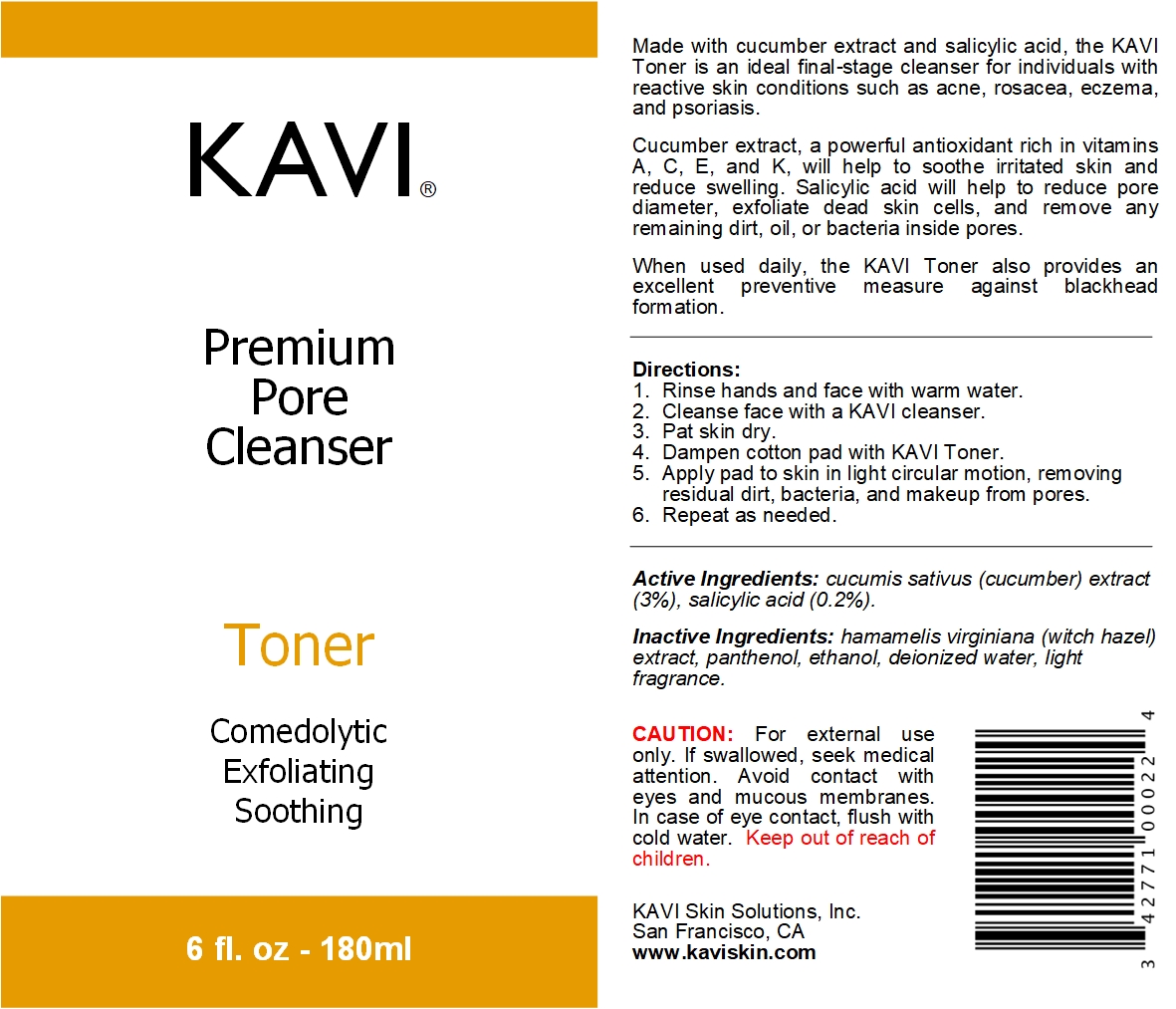 DRUG LABEL: Toner
NDC: 42771-0015 | Form: LIQUID
Manufacturer: KAVI Skin Solutions, Inc.
Category: otc | Type: HUMAN OTC DRUG LABEL
Date: 20201020

ACTIVE INGREDIENTS: SALICYLIC ACID 0.2 g/100 g
INACTIVE INGREDIENTS: CUCUMIS SATIVUS LEAF 3 g/100 g; PANTHENOL 0.5 g/100 g; 2,4-DIAMINOPHENOXYETHANOL SULFATE 70 g/100 g; WATER 16.3 g/100 g; HAMAMELIS VIRGINIANA LEAF 10 g/100 g

Toner

Dosage & Administration

Directions:
1. Rinse hands and face with warm water.
2. Cleanse face with a KAVI cleanser.
3. Pat skin dry.
4. Dampen cotton pad with KAVI Toner.
5. Apply pad to skin in light circular motion, removing residual dirt, bacteria, and makeup from pores.
6. Repeat as needed.

Purpose

Made with cucumber extract and salicylic acid, the KAVI Toner is an ideal final-stage cleanser for individuals with reactive skin conditions such as acne, rosacea, eczema, and psoriasis.
Cucumber extract, a powerful antioxidant rich in vitamins A, C, E, and K, will help to soothe irritated skin and reduce swelling. Salicylic acid will help to reduce pore diameter, exfoliate dead skin cells, and remove any remaining dirt, oil, or bacteria inside pores.
When used daily, the KAVI Toner also provides an excellent preventive measure against blackhead formation.

Indications & Usage

Made with cucumber extract and salicylic acid, the KAVI Toner is an ideal final-stage cleanser for individuals with reactive skin conditions such as acne, rosacea, eczema, and psoriasis.

Directions:
1. Rinse hands and face with warm water.
2. Cleanse face with a KAVI cleanser.
3. Pat skin dry.
4. Dampen cotton pad with KAVI Toner.
5. Apply pad to skin in light circular motion, removing residual dirt, bacteria, and makeup from pores.
6. Repeat as needed.

Active Ingredients

Active Ingredients: cucumis sativus (cucumber) extract (3%), salicylic acid (0.2%).

Inactive Ingredients

Inactive Ingredients: hamamelis virginiana (witch hazel) extract, panthenol, ethanol, deionized water, light fragrance.

Warnings

For external use only. If swallowed, seek medical attention. Avoid contact with eyes and mucous membranes. In case of eye contact, flush with cold water. Keep out of reach of children.

Keep out of reach of children

CAUTION: For external use only. If swallowed, seek medical attention. Avoid contact with eyes and mucous membranes. In case of eye contact, flush with cold water. Keep out of reach of children.

Front and Back Labels

Made with cucumber extract and salicylic acid, the KAVI Toner is an ideal final-stage cleanser for individuals with reactive skin conditions such as acne, rosacea, eczema, and psoriasis.
Cucumber extract, a powerful antioxidant rich in vitamins A, C, E, and K, will help to soothe irritated skin and reduce swelling. Salicylic acid will help to reduce pore diameter, exfoliate dead skin cells, and remove any remaining dirt, oil, or bacteria inside pores.
When used daily, the KAVI Toner also provides an excellent preventive measure against blackhead formation.

Directions:
1. Rinse hands and face with warm water.
2. Cleanse face with a KAVI cleanser.
3. Pat skin dry.
4. Dampen cotton pad with KAVI Toner.
5. Apply pad to skin in light circular motion, removing residual dirt, bacteria, and makeup from pores.
6. Repeat as needed.

Active Ingredients: cucumis sativus (cucumber) extract (3%), salicylic acid (0.2%).
Inactive Ingredients: hamamelis virginiana (witch hazel) extract, panthenol, ethanol, deionized water, light fragrance.

CAUTION: For external use only. If swallowed, seek medical attention. Avoid contact with eyes and mucous membranes. In case of eye contact, flush with cold water. Keep out of reach of children.

KAVI Skin Solutions, Inc.
San Francisco, CA
www.kaviskin.com